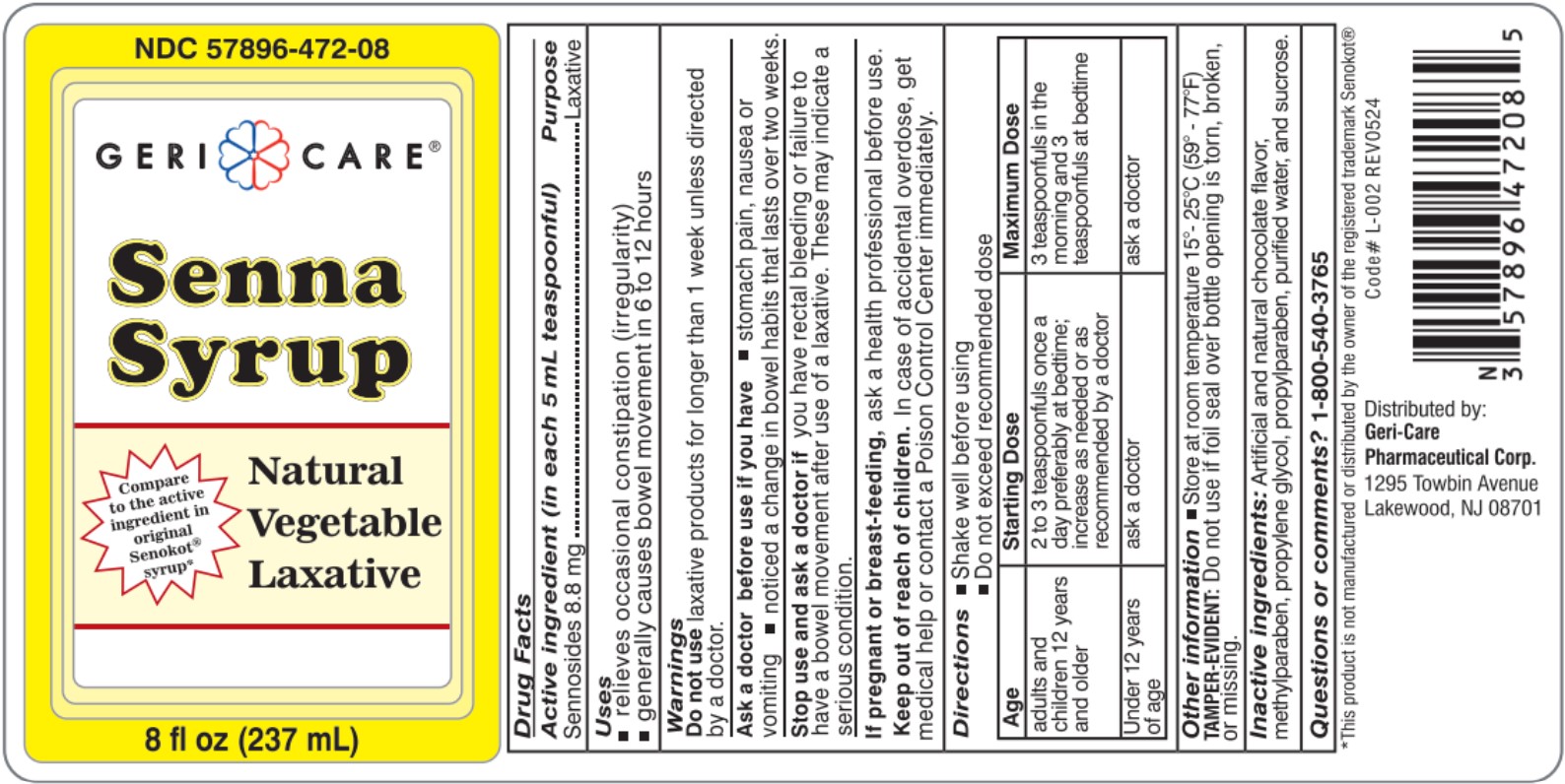 DRUG LABEL: GeriCare Senna Syrup
NDC: 57896-472 | Form: LIQUID
Manufacturer: Geri-Care Pharmaceutical Corp.
Category: otc | Type: HUMAN OTC DRUG LABEL
Date: 20251211

ACTIVE INGREDIENTS: SENNOSIDES 8.8 mg/5 mL
INACTIVE INGREDIENTS: METHYLPARABEN; PROPYLENE GLYCOL; PROPYLPARABEN; WATER; SUCROSE

Geri-Care Senna Syrup

Active ingredient (in each 5 ml teaspoonful): Sennosides 8.8 mg

PURPOSE

Laxative

INDICATIONS AND USAGE

- relieves occasional constipation (irregularity)
- generally causes bowel movement in 6 to 12 hours

Do not use

- laxative products for longer than 1 week unless directed by a doctor.

Ask a doctor or pharmacis before use if you have

- stomach pain, nausea or vomiting
- noticed a change in bowel habits that lasts over two weeks.

Stop use and ask a doctor if

you have rectal bleeding or failure to have a bowel movement after use of a laxative. These may indicate a serious condition.

PREGNANCY

If pregnant or breast-feeding, ask a health professional before use.

Keep out of reach of children. In case of accidental overdose, get medical help or contact a Poison Control Center immediately.

DOSAGE AND ADMINISTRATION

- Shake well before using
- Do not exceed recommended dose

Age | Starting Dose | Maximum Dose
adults and children 12 years and older | 2-3 teaspoonfuls once a day preferably at bedtime; increase as needed or as recommended by a doctor | 3 teaspoons in the morning and 3 teaspoons at bedtime
Under 12 years of age | ask a doctor | ask a doctor

STORAGE AND HANDLING

- Store at room temperature 15o - 25oC (59o - 77oF)

TAMPER-EVIDENT: Do not use if foil seal over bottle opening is torn, broken, or missing.

INACTIVE INGREDIENT

Inactive ingredients: Artificial and natural chocolate flavor, methylparaben, propylene glycol, propylparaben, purified water, and sucrose.

Questions or comments? 1-800-540-3765

PACKAGE LABEL

NDC 57896-472-08

Geri Care

Senna Syrup

Natural Vegetable Laxative

8 fl oz (237 mL)

Code# L-002

REV0524